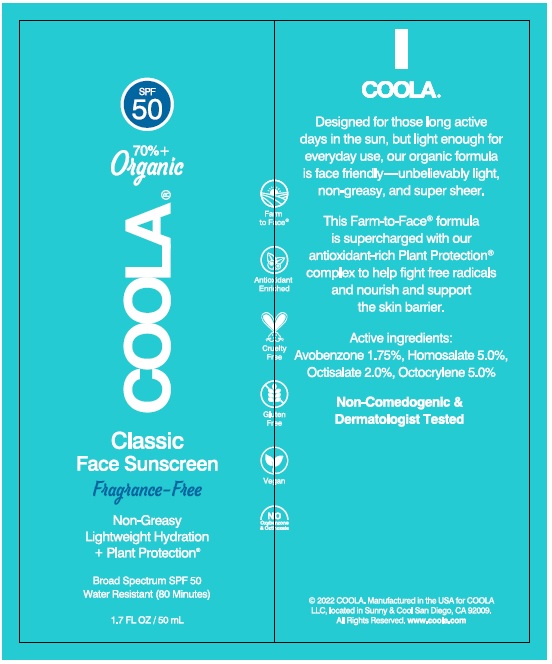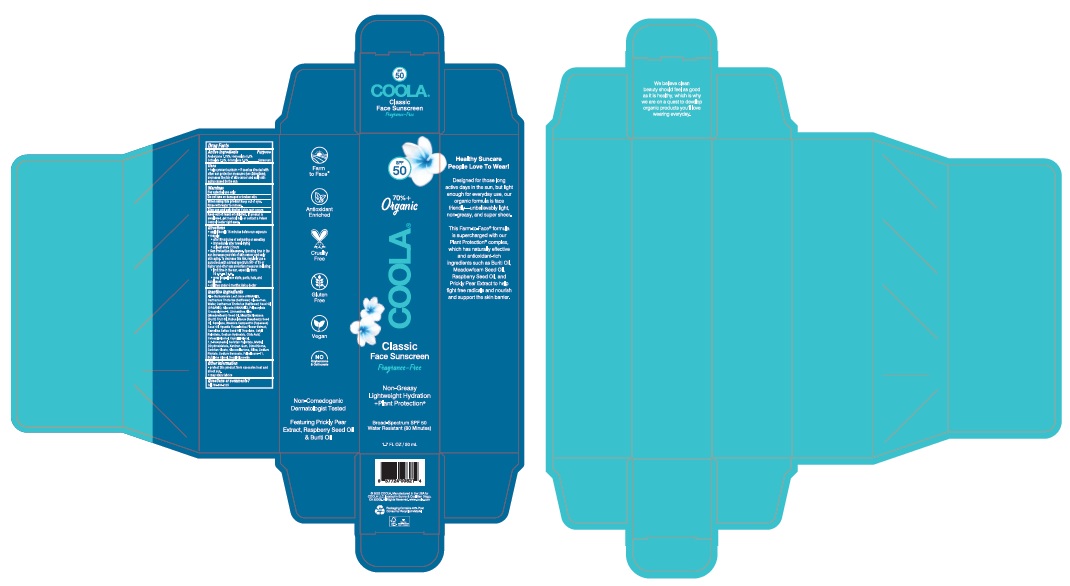 DRUG LABEL: COOLA Classic Face Sunscreen Fragrance-Free
NDC: 79753-074 | Form: LOTION
Manufacturer: COOLA LLC
Category: otc | Type: HUMAN OTC DRUG LABEL
Date: 20241227

ACTIVE INGREDIENTS: OCTISALATE 20 mg/1 mL; OCTOCRYLENE 50 mg/1 mL; HOMOSALATE 50 mg/1 mL; AVOBENZONE 17.5 mg/1 mL
INACTIVE INGREDIENTS: SODIUM HYDROXIDE; XANTHAN GUM; WATER; TROPOLONE; PHYTATE SODIUM; ALOE VERA LEAF; DECYL GLUCOSIDE; CITRIC ACID MONOHYDRATE; BUTYLENE GLYCOL; 1,2-HEXANEDIOL; SQUALANE; BRASSICA RAPA SUBSP. OLEIFERA OIL; CETOSTEARYL ALCOHOL; SORBITAN MONOPALMITATE; SORBITAN MONOOLEATE; METHYL DIHYDROABIETATE; SODIUM BENZOATE; RASPBERRY SEED OIL; DIMETHICONE/VINYL DIMETHICONE CROSSPOLYMER (SOFT PARTICLE); SILICON DIOXIDE; AMMONIUM ACRYLOYLDIMETHYLTAURATE, DIMETHYLACRYLAMIDE, LAURYL METHACRYLATE AND LAURETH-4 METHACRYLATE COPOLYMER, TRIMETHYLOLPROPANE TRIACRYLATE CROSSLINKED (45000 MPA.S); OPUNTIA FICUS-INDICA; GLUCONOLACTONE; CARTHAMUS TINCTORIUS SEEDCAKE; DIMETHICONE; MEADOWFOAM SEED OIL; GLYCERIN; SAFFLOWER OIL; CAPRYLYL GLYCOL; CAMELINA SATIVA SEED OIL

COOLA Classic Face Sunscreen Fragrance-Free SPF 50

Active Ingredients

AVOBENZONE 1.75%, HOMOSALATE 5.0%, OCTISALATE 2.0%, OCTOCRYLENE 5.0%

Purpose

Sunscreen

Uses
* helps prevent sunburn

* if used as directed with other sun protection measures (see Directions), decreases the rise of skin cancer and early skin aging caused by the sun

Warnings

For external use only

Do not use on damaged or broken skin

When using this product keep out of eyes. Rinse with water to remove

Stop use and ask doctor if skin rash occurs

Keep out of reach of children. If product is swallowed, get medical help or contact a Poison Control Center right away.

Directions

* apply liberally 15 minutes before sun exposure

* reapply:

* after 80 minutes of swimming or sweating

* immediately after towel drying

* at least every 2 hours

* Sun Protection Measures. Spending time in the sun increases your risk of skin cancer and early aging. To decrease this risk, regularly use a sunscreen with a broad spectrum SPF of 15 or higher and other sun protection measures including:
* limit time in the sun, especially from: 10 a.m. – 2 p.m.
* wear long-sleve shirts, pants, hats, and sunglasses

* children under 6 months: Ask a doctor

Inactive ingredients

Aloe Barbadensis Leaf Juice (ORGANIC),
Carthamus Tinctorius (Safflower) Oleosomes,
Water, Carthamus Tinctorius (Safflower) Seed Oil
(ORGANIC), Glycerin (ORGANIC), Polyacrylate
Crosspolymer-6, Limnanthes Alba
(Meadowfoam) Seed Oil, Mauritia Flexuosa
(Buriti) Fruit Oil, Rubus Idaeus (Raspberry) Seed
Oil, Squalane, Brassica Campestris (Rapeseed)
Seed Oil, Opuntia Ficus-Indica Flower Extract,
Camelina Sativa Seed Oil, Tropolone, Cetyl
Palmitate, Sodium Hydroxide, Citric Acid,
Cetearyl Alcohol, Caprylyl Glycol,
1,2-Hexanediol, Sorbitan Palmitate, Methyl
Dihydroabietate, Xanthan Gum, Dimethicone,
Sorbitan Oleate, Gluconolactone, Silica, Sodium
Phytate, Sodium Benzoate, Polysilicone-11,
Butylene Glycol, Decyl Glucoside

Other Information

* protect this product from excessive heat and direct sun

* may stain fabrics

Questions or comments? Call 760-940-2125

Product Labeling - COOLA Classic Face Sunscreen Fragrance-Free SPF 50

SPF
50

70% +
Organic

COOLA

Classic
Face Sunscreen
FragranceiFree

Broad Spectrum SPF 50
Water Resistant (80 Minutes)

1.7 FL OZ / 50 mL

2022 COOLA. Manufactured in the USA forDistributed by: COOLA LLC,

COOLA LLC, located in Sunny& Cool San Diego,

CA 92009. All Rights Reserved. ww.coola.com

Carton

Tube